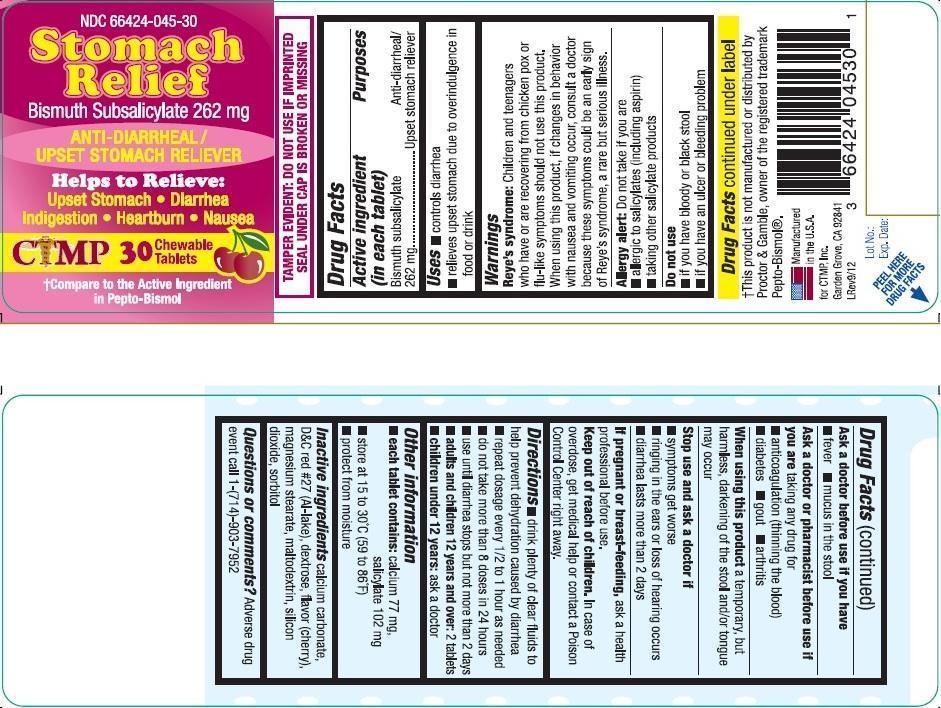 DRUG LABEL: Stomach Relief
NDC: 66424-045 | Form: TABLET, CHEWABLE
Manufacturer: SDA Laboratories, Inc.
Category: otc | Type: HUMAN OTC DRUG LABEL
Date: 20130803

ACTIVE INGREDIENTS: BISMUTH SUBSALICYLATE 262 mg/1 1
INACTIVE INGREDIENTS: CALCIUM CARBONATE; D&C RED NO. 27; DEXTROSE; MAGNESIUM STEARATE; MALTODEXTRIN; SILICON DIOXIDE; SORBITOL

Drug Facts

Active Ingredient (in each tablet)

Bismuth subsalicylate 262mg

Purposes

Anti-diarrheal/ Upset stomach reliever

Uses

- controls diarrhea
- relieves upset stomach due to overindulgence in food or drink

Warnings

Reye's syndrome: Children and teenagers who have or are recovering from chicken pox or flu-like symptoms should not use this product. When using this product, if changes in behavior with nausea and vomiting occur, consult a doctor because these symtoms could be an early sign of Reye's syndrome, a rare but serious illness.

Allergy alert: Do not take if you are

- allergic to salicylates (including aspirin)
- taking other salicylate products

Do not use

- if you have bloody or black stool
- if you have an ulcer or bleeding problem

Ask a doctor before use if you have

- fever
- mucus in the stool

Ask a doctor or pharmacist before use if you are

talking any drug for

- anticoagulation (thinning the blood)
- diabetes
- gout
- arthritis

When using this product

a temporary, but harmless, darkening of the stool and/or tongue may occur

Stop use and ask a doctor if

- symptoms get worse
- ringing in the ears or loss of hearing occurs
- diarrhea lasts more than 2 days

If pregnant or breast-feeding,

ask a health professional before use.

Keep out of reach of children

In case of overdose, get medical help or contact a Poison Control Center right away.

Directions

- drink plenty of clear fluids to help prevent dehydration caused by diarrhea
- repeat dosage every 1/2 to 1 hour as needed
- do not take more than 8 doses in 24 hours
- use untill diarrhea stops but not more than 2 days
- adults and children 12 years and over: 2 tablets
- children under 12 years: ask a doctor

Other information

- each tablet contains: calcium 77 mg, salicylate 102 mg
- store at 15 to 30^0C (59 to 86^0F)
- protect from moisture

Inactive ingredients

calcium carbonate, D&C red #27(Al-lake), dextrose, flavor(cherry), magnesium stearate, maltodextrin, silicon dioxide, sorbitol

Questions or comments?

Adverse drug event call 1-(714)-903-7952

Principal Display Panel

NDC 66424-045-30

Stomach Relief

Bismuth Subsalicylate 262 mg

Anti-Diarrheal/ Upset Stomach Reliever

Helps to Relieve:

- Upset Stomach
- Diarrhea
- Indigestion
- Heartburn
- Nausea

†Compare to the Active Ingredients in Pepto-Bismol

TAMPER EVIDENT: DO NOT USE IF IMPRINTED SEAL UNDER CAP IS BROKEN OR MISSING

†This product is not manufactured or distributed by Proctor & Gamble, owner of the registered trademark Pepto-Bismol